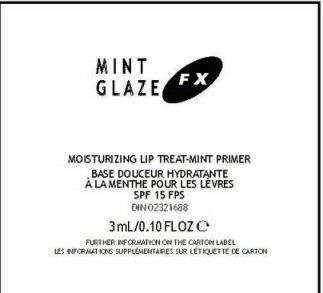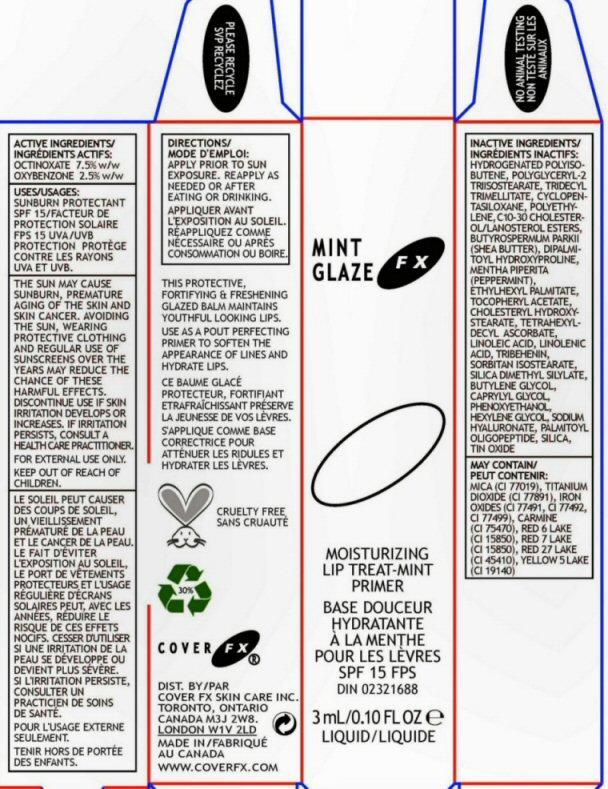 DRUG LABEL: Mint Glaze FX
NDC: 68327-004 | Form: OINTMENT
Manufacturer: Cover FX Skin Care, Inc.
Category: otc | Type: HUMAN OTC DRUG LABEL
Date: 20130219

ACTIVE INGREDIENTS: OCTINOXATE 7.5 g/100 mL; OXYBENZONE 2.5 g/100 mL
INACTIVE INGREDIENTS: HYDROGENATED POLYBUTENE (1300 MW); TRIDECYL TRIMELLITATE; CYCLOMETHICONE 5; HIGH DENSITY POLYETHYLENE; C10-30 CHOLESTEROL/LANOSTEROL ESTERS ; SHEA BUTTER; DIPALMITOYL HYDROXYPROLINE; MENTHA PIPERITA; ETHYLHEXYL PALMITATE; ALPHA-TOCOPHEROL ACETATE; CHOLESTERYL HYDROXYSTEARATE; TETRAHEXYLDECYL ASCORBATE; LINOLEIC ACID; LINOLENIC ACID; TRIBEHENIN; SORBITAN ISOSTEARATE; SILICA DIMETHYL SILYLATE; BUTYLENE GLYCOL; CAPRYLYL GLYCOL; PHENOXYETHANOL; HEXYLENE GLYCOL; HYALURONATE SODIUM; PALMITOYL OLIGOPEPTIDE; SILICON DIOXIDE; STANNIC OXIDE; MICA; TITANIUM DIOXIDE; FERRIC OXIDE RED; COCHINEAL; D&C RED NO. 6; D&C RED NO. 7; D&C RED NO. 27; FD&C YELLOW NO. 5

Active Ingredient Section

ACTIVE INGREDIENTS; OCTINOXATE 7.5% w/w OXYBENZONE 2.5% w/w

Purpose Section

MOISTURIZING LIP TREAT-MINT PRIMER SPF 15

THIS PROTECTIVE FORTIFYING AND FRESHENING GLAZED BALM MAINTAINS YOUTHFUL LOOKING LIPS.

USE AS A POUT PERFECTING PRIMER TO SOFTEN THE APPEARANCE OF LINES AND HYDRATE LIPS.

Keep Out of Reach of Children Section

KEEP OUT OF REACH OF CHILDREN

Uses Section

USES: SUNBURN PROTECTANT SPF 15

Warnings Section

THE SUN MAY CAUSE SUNBURN, PREMATURE AGING OF THE SKIN AND SKIN CANCER. AVOIDING THE SUN, WEARING PROTECTIVE CLOTHING AND THE REGULAR USE OF SUNSCREENS OVER THE YEARS MAY REDUCE THE CHANCE OF THESE HARMFUL EFFECTS. DISCONTINUE USE IF SKIN IRRITATION DEVELOPS OR INCREASES. IF IRRITATION PERSISTS, CONSULT A HEALTH CARE PRACTITIONER. FOR EXTERNAL USE ONLY.

Directions Section

DIRECTIONS APPLY PRIOR TO SUN EXPOSURE. REAPPLY AS NEEDED OR AFTER EATING AND DRINKING.

Inactive Ingredient Section

INACTIVE INGREDIENTS: HYDROGENATED POLYISOBUTENE, POLYGLCERYL-2 TRIISOSTEARATE, TRIDECYL TRIMELLITATE, CYCLOPENTASILOXANE, POLYETHYLENE, C10-30 CHOLESTEROL/LANOSTEROL ESTERS, BUTYROSPERMUM PARKII (SHEA BUTTER), DIPALMITOYL HYDROXYPROLINE, MENTHA PIPERITA (PEPPERMINT), ETHYLHEXYL PALMITATE, TOCOPHERYL ACETATE, CHOLESTERYL HYDROXYSTEARATE, TETRAHEXYLDECYL ASCORBATE, LINOLEIC ACID, LINOLENIC ACID, TRIBEHENIN, SORBITAN ISOSTERATE, SILICA DIMETHYL SILYLATE, BUTYLENE GLYCOL, CAPRYLYL GLYCOL, PHENOXYETHANOL, HEXYLENE GLYCOL, SODIUM HYALURONATE, PALMITOYL OLIGOPEPTIDE, SILICA, TIN OXIDE

MAY CONTAIN: MICA (CI 77499), TITANIUM DIOXIDE (CI 77891), IRON OXIDES (CI 77491, CI 77492, CI 77499), CARMINE (CI 75470), RED 6 LAKE (CI 15850), RED 7 LAKE (CI 15850), RED 27 LAKE (CI 45410), YELLOW 5 LAKE (CI 19140)

Package Label Section

MINT GLAZE FX

3 ml/0.10 FL OZ LIQUID CRUELTY FREE NO ANIMAL TESTING 30 PERCENT RECYCLE PLEASE RECYCLE

COVER FX DIST. BY COVER FX SKIN CARE INC. TORONTO, ONTARIO CANADA M3J 2W8. WWW.COVERFX.COM